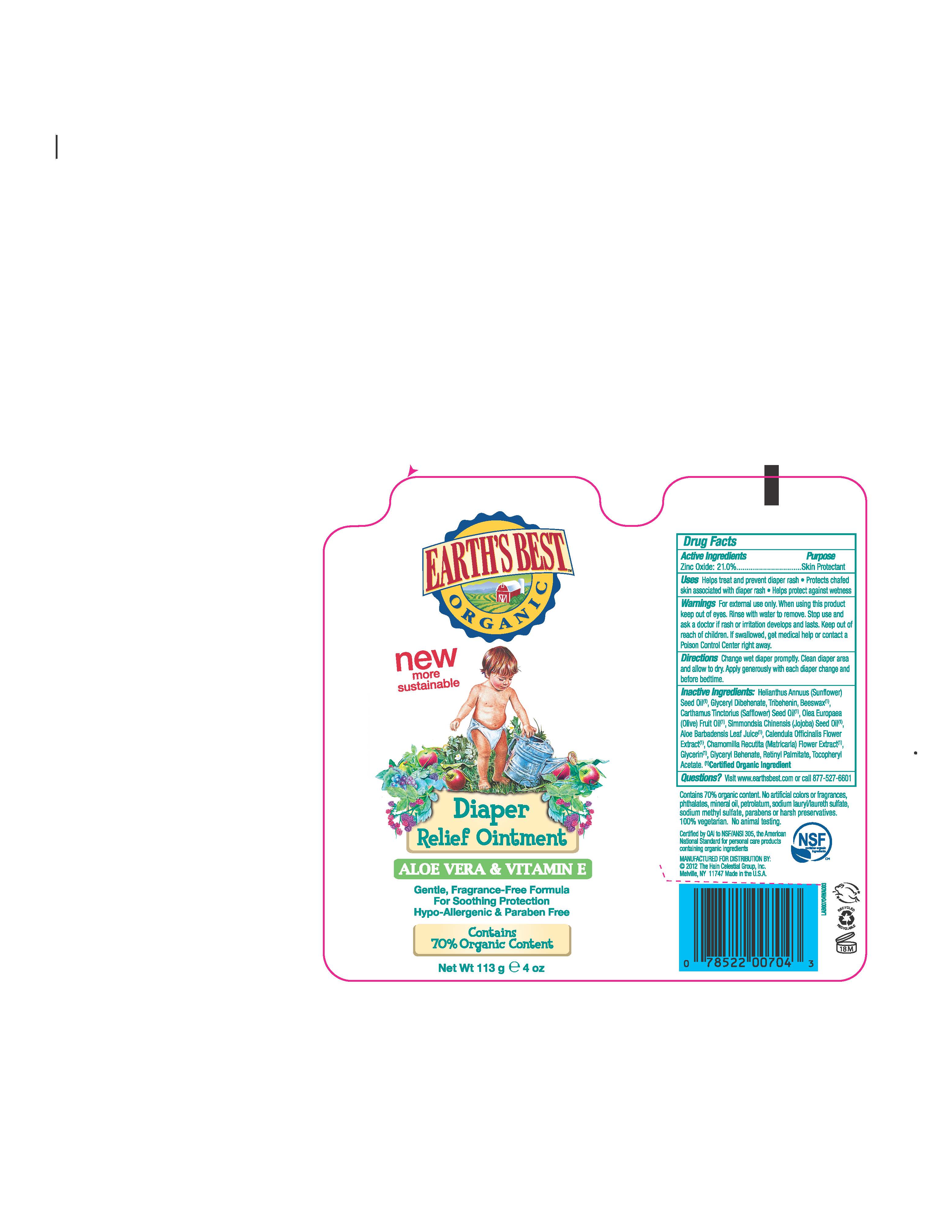 DRUG LABEL:  Earths Best Diaper Relief 
NDC: 61995-0405 | Form: OINTMENT
Manufacturer: The Hain Celestial Group, Inc
Category: otc | Type: HUMAN OTC DRUG LABEL
Date: 20120522

ACTIVE INGREDIENTS: Zinc Oxide 21 g/100 g
INACTIVE INGREDIENTS: SUNFLOWER OIL; TRIBEHENIN; WHITE WAX; GLYCERYL DIBEHENATE; SAFFLOWER OIL; OLIVE OIL; JOJOBA OIL ; ALOE VERA LEAF; CALENDULA OFFICINALIS FLOWER ; CHAMOMILE; GLYCERIN; VITAMIN A PALMITATE; .ALPHA.-TOCOPHEROL ACETATE

Drug Facts

ACTIVE INGREDIENT

Zinc Oxide 21.0%

PURPOSE

Natural Skin Protectant

INDICATIONS AND USAGE

- Helps treat and prevent diaper rash.
- Protects chafed skin associated with diaper rash.
- Helps protect against wetness

When using this product keep out of eyes. Rinse with water to remove. Stop use and ask doctor if rash or irritation develops and lasts.

Keep out of reach of children. If swallowed get medical help or contact Poison Center right away.

DOSAGE AND ADMINISTRATION

- Change wet diaper promptly. Clean diaper area and allow to dry. Apply generously with each diaper change and before bedtime.

INACTIVE INGREDIENT

Helianthus Annuus (Sunflower) Seed Oil *, Glyceryl Dibehenate, Tribehenin, Beeswax*, Carthamus Tinctorius (Safflower) Oil* , Olea Europea (Olive) Fruit Oil *, Simmondsia Chinensis (Jojoba) Seed Oil*, Aloe Barbadensis Leaf Juice* , Calendula Officinalis Flower Extract* , Chamomilla Recutita (Matricaria) Flower Extract *, Glycerin *, Glyceryl Behenate, Retinyl Palmitate, Tocopheryl Acetate.

* Certified Organic Ingredients

QUESTIONS

Questions? Visit www.earthsbest.com or call 877-527-6801